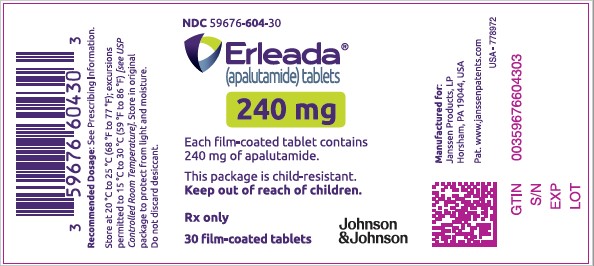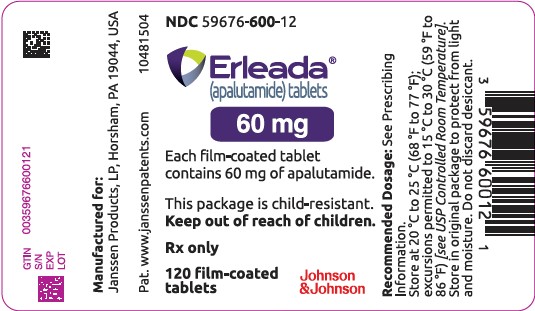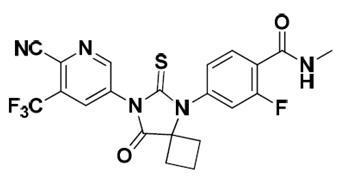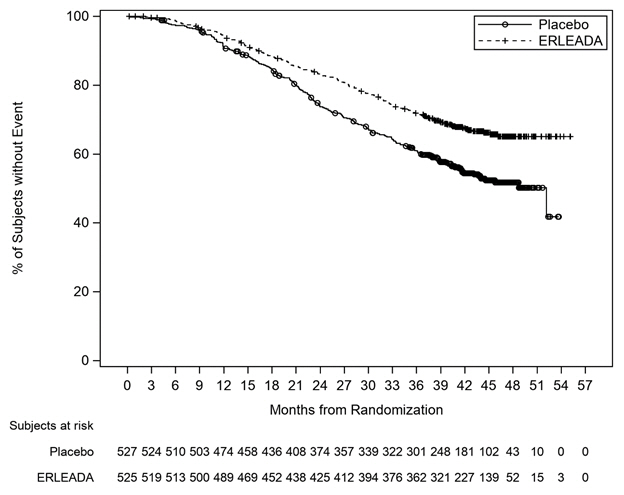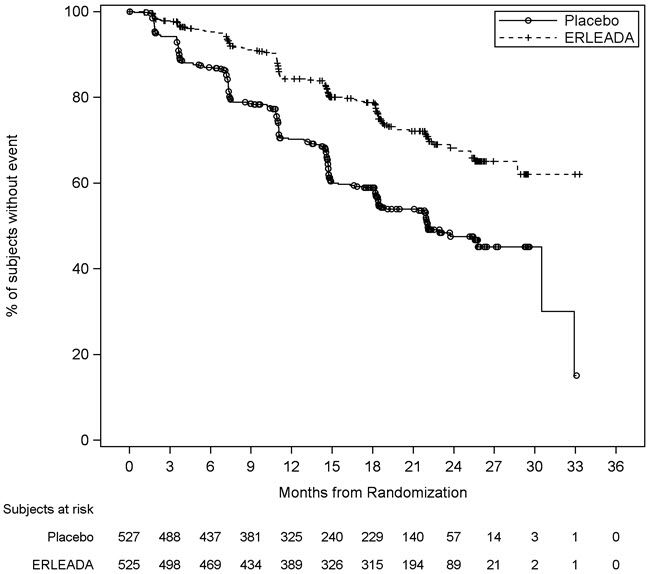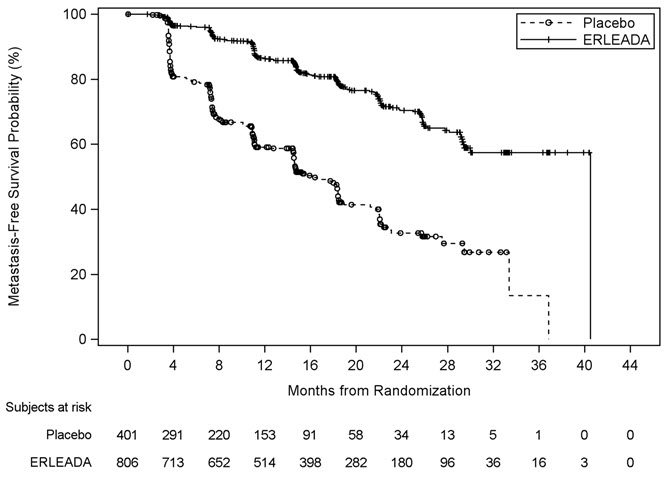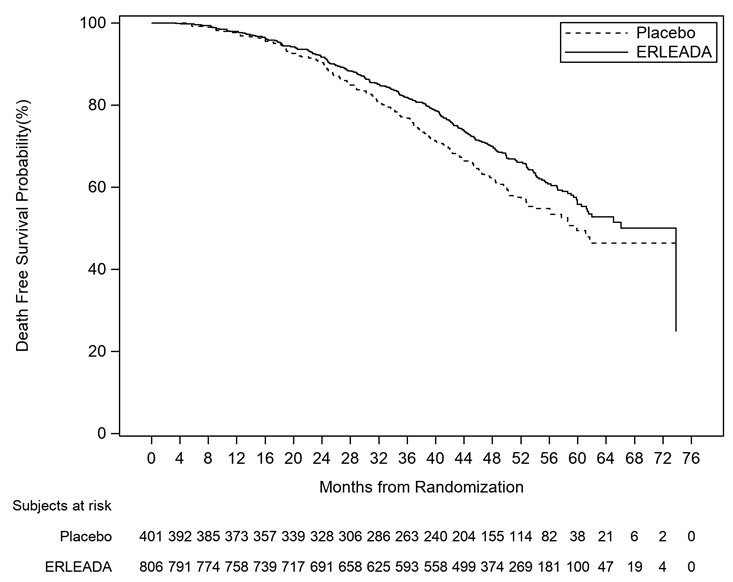 DRUG LABEL: ERLEADA
NDC: 59676-600 | Form: TABLET, FILM COATED
Manufacturer: Janssen Products, LP
Category: prescription | Type: HUMAN PRESCRIPTION DRUG LABEL
Date: 20250909

ACTIVE INGREDIENTS: APALUTAMIDE 60 mg/1 1
INACTIVE INGREDIENTS: CROSCARMELLOSE SODIUM; HYPROMELLOSE ACETATE SUCCINATE 16070722 (3 MPA.S); MAGNESIUM STEARATE; MICROCRYSTALLINE CELLULOSE; FERROSOFERRIC OXIDE; FERRIC OXIDE YELLOW; POLYETHYLENE GLYCOL, UNSPECIFIED; POLYVINYL ALCOHOL, UNSPECIFIED; TALC; TITANIUM DIOXIDE; SILICON DIOXIDE

HIGHLIGHTS OF PRESCRIBING INFORMATION

These highlights do not include all the information needed to use ERLEADA safely and effectively. See full prescribing information for ERLEADA.
ERLEADA®(apalutamide) tablets, for oral use
Initial U.S. Approval – 2018

RECENT MAJOR CHANGES

Dosage and Administration, Recommended Dosage (2.1) | 8/2024
Dosage and Administration, Dosage Modification (2.2) | 8/2024
Dosage and Administration, Alternate Methods of Administration (2.3) | 8/2024
Warnings and Precautions, Interstitial Lung Disease (ILD) (5.6) | 8/2024

1 INDICATIONS AND USAGE

ERLEADA is an androgen receptor inhibitor indicated for the treatment of patients with

- metastatic castration-sensitive prostate cancer. (1)
- non-metastatic castration-resistant prostate cancer. (1)

2 DOSAGE AND ADMINISTRATION

ERLEADA 240 mg administered orally once daily. Swallow tablets whole. ERLEADA can be taken with or without food. (2.1, 2.3)

Patients should also receive a gonadotropin-releasing hormone (GnRH) analog concurrently or should have had bilateral orchiectomy. (2.1)

3 DOSAGE FORMS AND STRENGTHS

Tablets: 240 mg (3)

Tablets: 60 mg (3)

4 CONTRAINDICATIONS

None. (4)

5 WARNINGS AND PRECAUTIONS

- Cerebrovascular and ischemic cardiovascular events occurred in patients receiving ERLEADA. Monitor for signs and symptoms of cerebrovascular disorders and ischemic heart disease. Optimize management of cardiovascular risk factors. (5.1).
- Fractures occurred in patients receiving ERLEADA. Evaluate patients for fracture risk and treat patients with bone-targeted agents according to established guidelines. (5.2)
- Falls occurred in patients receiving ERLEADA with increased incidence in the elderly. Evaluate patients for fall risk. (5.3)
- Seizure occurred in 0.4% of patients receiving ERLEADA. Permanently discontinue ERLEADA in patients who develop a seizure during treatment. (5.4)
- Severe Cutaneous Adverse Reactions (SCARs), including Stevens-Johnson syndrome/toxic epidermal necrolysis (SJS/TEN) and drug reaction with eosinophilia and systemic symptoms (DRESS), occurred in patients treated with ERLEADA. Interrupt ERLEADA if signs or symptoms of SCARs develop. Permanently discontinue if SCARs are confirmed. (5.5)
- Interstitial Lung Disease (ILD)/pneumonitis occurred in patients treated with ERLEADA. Withhold ERLEADA for suspected ILD/pneumonitis. Permanently discontinue ERLEADA in patients with severe ILD/pneumonitis or if no other potential causes of ILD/pneumonitis are identified. (2.2, 5.6)
- Embryo-Fetal Toxicity: ERLEADA can cause fetal harm. Advise males with female partners of reproductive potential to use effective contraception. (5.7, 8.1, 8.3)

6 ADVERSE REACTIONS

The most common adverse reactions (≥10%) are fatigue, arthralgia, rash, decreased appetite, fall, weight decreased, hypertension, hot flush, diarrhea, and fracture. (6.1)

To report SUSPECTED ADVERSE REACTIONS, contact Janssen Products, LP at 1-800-526-7736 (1-800-JANSSEN) or FDA at 1-800-FDA-1088 or www.fda.gov/medwatch.

7 DRUG INTERACTIONS

Concomitant use with medications that are sensitive substrates of CYP3A4, CYP2C19, CYP2C9, UGT, P-gp, BCRP, or OATP1B1 may result in loss of activity of these medications. (7.2)

FULL PRESCRIBING INFORMATION

1 INDICATIONS AND USAGE

ERLEADA is indicated for the treatment of patients with

- Metastatic castration-sensitive prostate cancer (mCSPC)
- Non-metastatic castration-resistant prostate cancer (nmCRPC)

2 DOSAGE AND ADMINISTRATION

2.1 Recommended Dosage

The recommended dose of ERLEADA is 240 mg administered orally once daily. This could be administered as one 240 mg tablet or four 60 mg tablets. Swallow the tablet(s) whole. Do not crush or split tablet(s). ERLEADA can be taken with or without food.

Patients should also receive a gonadotropin-releasing hormone (GnRH) analog concurrently or should have had a bilateral orchiectomy.

2.2 Dosage Modification

If Grade 3 or greater adverse reactions, or other intolerable adverse reactions occur, withhold ERLEADA. Consider permanent discontinuation of ERLEADA for Grade 3 or 4 cerebrovascular and ischemic cardiovascular events [see Warnings and Precautions (5.1)] . Permanently discontinue ERLEADA for severe ILD/pneumonitis or if no other potential causes of ILD/pneumonitis are identified, or confirmed SCARs, or for other Grade 4 skin reactions [see Warnings and Precautions (5.5, 5.6)and Adverse Reactions (6.1)] . For other adverse reactions, when symptoms improve to less than or equal to Grade 1 or original grade, resume ERLEADA at the same dose or a reduced dose (180 mg or 120 mg), if warranted.

2.3 Alternate Methods of Administration

Disperse Tablet(s) in Water and Administer with Orange Juice, Applesauce, or Additional Water

For patients who cannot swallow tablets whole, the recommended dose of ERLEADA tablet(s) can be dispersed in non-carbonated water and then administered with either orange juice, applesauce, or additional water as follows:

1. Place the entire prescribed dose of ERLEADA tablet(s) in a cup. Do not crush or split the tablet(s).
2. For one 240 mg tablet:Add about 2 teaspoons (10 mL) of non-carbonated water to make sure that the tablet is completely immersed in water.
  For 60 mg tablets (prescribed dose of 240 mg, 180 mg, or 120 mg):Add about 4 teaspoons (20 mL) of non-carbonated water to make sure that the tablets are completely immersed in water.
3. Wait 2 minutes until the tablet(s) are broken up and spread out, then stir the mixture.
4. Add 2 tablespoons (30 mL) of either orange juice, applesauce, or additional water and stir the mixture.
5. Swallow the mixture immediately.
6. Rinse the cup with enough water to make sure the whole dose is taken and drink it immediately.

Do not store ERLEADA that is mixed with non-carbonated water, orange juice, or applesauce for later use.

Administer Tablet(s) Through a Feeding Tube

ERLEADA tablet(s) can be administered through a feeding tube 8 French or greater as follows:

1. For one 240 mg tablet:Place the tablet in the barrel of the syringe (use at least a 20 mL syringe) and draw up 10 mL of non-carbonated water into the syringe.
  For 60 mg tablets (prescribed dose of 240 mg, 180 mg, or 120 mg):Place the entire prescribed dose of ERLEADA tablets in the barrel of the syringe (use at least a 50 mL syringe) and draw up 20 mL of non-carbonated water into the syringe.
2. Wait 10 minutes and then shake vigorously to disperse contents completely.
3. Administer immediately through the feeding tube.
4. Refill the syringe with non-carbonated water and administer. Repeat until no tablet residue is left in the syringe or feeding tube.

3 DOSAGE FORMS AND STRENGTHS

Tablets:

- 240 mg: bluish grey to grey, oval, film-coated and debossed with "E240" on one side.
- 60 mg: slightly yellowish to greyish green, oblong, film-coated and debossed with "AR 60" on one side.

4 CONTRAINDICATIONS

None.

5 WARNINGS AND PRECAUTIONS

5.1 Cerebrovascular and Ischemic Cardiovascular Events

Cerebrovascular and ischemic cardiovascular events, including events leading to death, occurred in patients receiving ERLEADA. Monitor for signs and symptoms of ischemic heart disease and cerebrovascular disorders. Optimize management of cardiovascular risk factors, such as hypertension, diabetes, or dyslipidemia. Consider discontinuation of ERLEADA for Grade 3 and 4 events.

In a randomized study (SPARTAN) of patients with nmCRPC, ischemic cardiovascular events occurred in 3.7% of patients treated with ERLEADA and 2% of patients treated with placebo. In a randomized study (TITAN) in patients with mCSPC, ischemic cardiovascular events occurred in 4.4% of patients treated with ERLEADA and 1.5% of patients treated with placebo. Across the SPARTAN and TITAN studies, 4 patients (0.3%) treated with ERLEADA, and 2 patients (0.2%) treated with placebo died from an ischemic cardiovascular event.

In the SPARTAN study, cerebrovascular events occurred in 2.5% of patients treated with ERLEADA and 1% of patients treated with placebo [see Adverse Reactions (6.1)] . In the TITAN study, cerebrovascular events occurred in 1.9% of patients treated with ERLEADA and 2.1% of patients treated with placebo. Across the SPARTAN and TITAN studies, 3 patients (0.2%) treated with ERLEADA, and 2 patients (0.2%) treated with placebo died from a cerebrovascular event.

Patients with history of unstable angina, myocardial infarction, congestive heart failure, stroke, or transient ischemic attack within six months of randomization were excluded from the SPARTAN and TITAN studies.

5.2 Fractures

Fractures occurred in patients receiving ERLEADA. Evaluate patients for fracture risk. Monitor and manage patients at risk for fractures according to established treatment guidelines and consider use of bone-targeted agents.

In a randomized study (SPARTAN) of patients with non-metastatic castration-resistant prostate cancer, fractures occurred in 12% of patients treated with ERLEADA and in 7% of patients treated with placebo. Grade 3–4 fractures occurred in 2.7% of patients treated with ERLEADA and in 0.8% of patients treated with placebo. The median time to onset of fracture was 314 days (range: 20 to 953 days) for patients treated with ERLEADA. Routine bone density assessment and treatment of osteoporosis with bone-targeted agents were not performed in the SPARTAN study.

In a randomized study (TITAN) of patients with metastatic castration-sensitive prostate cancer, fractures occurred in 9% of patients treated with ERLEADA and in 6% of patients treated with placebo. Grade 3–4 fractures were similar in both arms at 1.5%. The median time to onset of fracture was 56 days (range: 2 to 111 days) for patients treated with ERLEADA. Routine bone density assessment and treatment of osteoporosis with bone-targeted agents were not performed in the TITAN study.

5.3 Falls

Falls occurred in patients receiving ERLEADA with increased frequency in the elderly [see Use in Specific Populations (8.5)] . Evaluate patients for fall risk.

In a randomized study (SPARTAN), falls occurred in 16% of patients treated with ERLEADA compared to 9% of patients treated with placebo. Falls were not associated with loss of consciousness or seizure.

5.4 Seizure

Seizure occurred in patients receiving ERLEADA. Permanently discontinue ERLEADA in patients who develop a seizure during treatment. It is unknown whether anti-epileptic medications will prevent seizures with ERLEADA. Advise patients of the risk of developing a seizure while receiving ERLEADA and of engaging in any activity where sudden loss of consciousness could cause harm to themselves or others.

In two randomized studies (SPARTAN and TITAN), five patients (0.4%) treated with ERLEADA and one patient treated with placebo (0.1%) experienced a seizure. Seizure occurred from 159 to 650 days after initiation of ERLEADA. Patients with a history of seizure, predisposing factors for seizure, or receiving drugs known to decrease the seizure threshold or to induce seizure were excluded. There is no clinical experience in re-administering ERLEADA to patients who experienced a seizure.

5.5 Severe Cutaneous Adverse Reactions

Fatal and life-threatening cases of severe cutaneous adverse reactions (SCARs), including Stevens-Johnson syndrome/toxic epidermal necrolysis (SJS/TEN), and drug reaction with eosinophilia and systemic symptoms (DRESS), occurred in patients receiving ERLEADA [see Adverse Reactions (6.2)] .

Monitor patients for the development of SCARs. Advise patients of the signs and symptoms of SCARs (e.g., a prodrome of fever, flu-like symptoms, mucosal lesions, progressive skin rash, or lymphadenopathy).

If a SCAR is suspected, interrupt ERLEADA until the etiology of the reaction has been determined. Consultation with a dermatologist is recommended. If a SCAR is confirmed, or for other grade 4 skin reactions, permanently discontinue ERLEADA [see Dosage and Administration (2.2)and Adverse Reactions (6.1)] .

5.6 Interstitial Lung Disease (ILD)/Pneumonitis

Fatal and life-threatening interstitial lung disease (ILD) or pneumonitis can occur in patients treated with ERLEADA.

Post-marketing cases of ILD/pneumonitis, including fatal cases, occurred in patients treated with ERLEADA. Across clinical trials (TITAN and SPARTAN, n=1327), 0.8% of patients treated with ERLEADA experienced ILD/pneumonitis, including 0.2% who experienced Grade 3 events [see Adverse Reactions (6.1, 6.2)].

Monitor patients for new or worsening symptoms indicative of ILD/pneumonitis (e.g., dyspnea, cough, fever). Immediately withhold ERLEADA if ILD/pneumonitis is suspected.

Permanently discontinue ERLEADA in patients with severe ILD/pneumonitis or if no other potential causes of ILD/pneumonitis are identified [see Dosage and Administration (2.2)] .

5.7 Embryo-Fetal Toxicity

The safety and efficacy of ERLEADA have not been established in females. Based on findings from animals and its mechanism of action, ERLEADA can cause fetal harm and loss of pregnancy when administered to a pregnant female. In an animal reproduction study, oral administration of apalutamide to pregnant rats during and after organogenesis resulted in fetal abnormalities and embryo-fetal lethality at maternal exposures ≥ 2 times the human clinical exposure (AUC) at the recommended dose. Advise males with female partners of reproductive potential to use effective contraception during treatment and for 3 months after the last dose of ERLEADA [see Use in Specific Populations (8.1, 8.3)and Clinical Pharmacology (12.1)] .

6 ADVERSE REACTIONS

The following are discussed in more detail in other sections of the labeling:

- Cerebrovascular and Ischemic Cardiovascular Events [see Warnings and Precautions (5.1)] .
- Fractures [see Warnings and Precautions (5.2)] .
- Falls [see Warnings and Precautions (5.3)] .
- Seizure [see Warnings and Precautions (5.4)] .
- Severe Cutaneous Adverse Reactions (SCARs) [see Warnings and Precautions (5.5)] .
- Interstitial Lung Disease (ILD) [see Warnings and Precautions (5.6)] .

6.1 Clinical Trial Experience

Because clinical trials are conducted under widely varying conditions, adverse reaction rates observed in the clinical trials of a drug cannot be directly compared to rates in the clinical trials of another drug and may not reflect the rates observed in practice.

The most common adverse reactions (≥ 10%) that occurred more frequently in the ERLEADA-treated patients (≥ 2% over placebo) from the randomized placebo-controlled clinical trials (TITAN and SPARTAN) were fatigue, arthralgia, rash, decreased appetite, fall, weight decreased, hypertension, hot flush, diarrhea, and fracture.

Metastatic Castration-sensitive Prostate Cancer (mCSPC)

TITAN, a randomized (1:1), double-blind, placebo-controlled, multi-center clinical study, enrolled patients who had mCSPC. In this study, patients received either ERLEADA at a dose of 240 mg daily or placebo. All patients in the TITAN study received a concomitant gonadotropin-releasing hormone (GnRH) analog or had prior bilateral orchiectomy. The median duration of exposure was 20 months (range: 0 to 34 months) in patients who received ERLEADA and 18 months (range: 0.1 to 34 months) in patients who received placebo.

Ten patients (1.9%) who were treated with ERLEADA died from adverse reactions. The reasons for death were ischemic cardiovascular events (n=3), acute kidney injury (n=2), cardio-respiratory arrest (n=1), sudden cardiac death (n=1), respiratory failure (n=1), cerebrovascular accident (n=1), and large intestinal ulcer perforation (n=1). ERLEADA was discontinued due to adverse reactions in 8% of patients, most commonly from rash (2.3%). Adverse reactions leading to dose interruption or reduction of ERLEADA occurred in 23% of patients; the most frequent (>1%) were rash, fatigue, and hypertension. Serious adverse reactions occurred in 20% of ERLEADA-treated patients and 20% in patients receiving placebo.

Table 1 shows adverse reactions occurring in ≥10% on the ERLEADA arm in TITAN that occurred with a ≥2% absolute increase in frequency compared to placebo. Table 2 shows laboratory abnormalities that occurred in ≥15% of patients, and more frequently (>5%) in the ERLEADA arm compared to placebo.

Table 1: Adverse Reactions in TITAN (mCSPC)
 | ERLEADA N=524 |  | Placebo N=527
System/Organ Class Adverse reaction | All Grades % | Grade 3–4 % | All Grades % | Grade 3–4 %
Musculoskeletal and connective tissue disorders
Arthralgia [Per the Common Terminology Criteria for Adverse Reactions (CTCAE), the highest severity for these events is Grade 3] | 17 | 0.4 | 15 | 0.9
Skin and subcutaneous tissue disorders
Rash [Includes rash, rash maculo-papular, rash generalized, urticaria, rash pruritic, rash macular, conjunctivitis, erythema multiforme, rash papular, skin exfoliation, genital rash, rash erythematous, stomatitis, drug eruption, mouth ulceration, rash pustular, blister, papule, pemphigoid, skin erosion, dermatitis, and rash vesicular] | 28 | 6 | 9 | 0.6
Pruritus | 11 | 0.2 | 4.6 | 0.2
Vascular disorders
Hot flush | 23 | 0 | 16 | 0
Hypertension | 18 | 8 | 16 | 9

Additional adverse reactions of interest occurring in less than 10% of patients treated with ERLEADA included diarrhea (9% versus 6% on placebo), muscle spasm (3.1% versus 1.9% on placebo), dysgeusia (3.2% versus 0.6% on placebo), hypothyroidism (3.6% versus 0.6% on placebo), and ILD/pneumonitis (1.1% versus 0.4% on placebo).

Table 2: Laboratory Abnormalities Occurring in ≥ 15% of ERLEADA-Treated Patients and at a Higher Incidence than Placebo (Between Arm Difference > 5% All Grades) in TITAN (mCSPC)
 | ERLEADA N=524 |  | Placebo N=527
Laboratory Abnormality | All Grades % | Grade 3–4 % | All Grades % | Grade 3–4 %
Hematology
White blood cell decreased | 27 | 0.4 | 19 | 0.6
Chemistry
Hypertriglyceridemia [Does not reflect fasting values] | 17 | 2.5 | 12 | 2.3

Non-metastatic Castration-resistant Prostate Cancer (nmCRPC)

SPARTAN, a randomized (2:1), double-blind, placebo-controlled, multi-center clinical study, enrolled patients who had nmCRPC. In this study, patients received either ERLEADA at a dose of 240 mg daily or a placebo. All patients in the SPARTAN study received a concomitant gonadotropin-releasing hormone (GnRH) analog or had a bilateral orchiectomy. The median duration of exposure was 33 months (range: 0.1 to 75 months) in patients who received ERLEADA and 11 months (range: 0.1 to 37 months) in patients who received placebo.

Twenty-four patients (3%) who were treated with ERLEADA died from adverse reactions. The reasons for death with ≥ 2 patients included infection (n=7), myocardial infarction (n=3), cerebrovascular event (n=2), and unknown reason (n=3). ERLEADA was discontinued due to adverse reactions in 11% of patients, most commonly from rash (3.2%). Adverse reactions leading to dose interruption or reduction of ERLEADA occurred in 33% of patients; the most common (>1%) were rash, diarrhea, fatigue, nausea, vomiting, hypertension, and hematuria. Serious adverse reactions occurred in 25% of ERLEADA-treated patients and 23% in patients receiving placebo. The most frequent serious adverse reactions (>2%) were fracture (3.4%) in the ERLEADA arm and urinary retention (3.8%) in the placebo arm.

Table 3 shows adverse reactions occurring in ≥10% on the ERLEADA arm in SPARTAN that occurred with a ≥2% absolute increase in frequency compared to placebo. Table 4 shows laboratory abnormalities that occurred in ≥15% of patients, and more frequently (>5%) in the ERLEADA arm compared to placebo.

Table 3: Adverse Reactions in SPARTAN (nmCRPC)
 | ERLEADA N=803 |  | Placebo N=398
System/Organ Class Adverse reaction | All Grades % | Grade 3–4 % | All Grades % | Grade 3–4 %
General disorders and administration site conditions
Fatigue [Includes fatigue and asthenia] , [Per the Common Terminology Criteria for Adverse Reactions (CTCAE), the highest severity for these events is Grade 3] | 39 | 1.4 | 28 | 0.3
Musculoskeletal and connective tissue disorders
Arthralgia | 16 | 0 | 8 | 0
Skin and subcutaneous tissue disorders
Rash [Includes rash, rash maculo-papular, rash generalized, urticaria, rash pruritic, rash macular, conjunctivitis, erythema multiforme, rash papular, skin exfoliation, genital rash, rash erythematous, stomatitis, drug eruption, mouth ulceration, rash pustular, blister, papule, pemphigoid, skin erosion, dermatitis, and rash vesicular] | 25 | 5.2 | 6 | 0.3
Metabolism and nutrition disorders
Decreased appetite [Includes appetite disorder, decreased appetite, early satiety, and hypophagia] | 12 | 0.1 | 9 | 0
Peripheral edema [Includes peripheral edema, generalized edema, edema, edema genital, penile edema, peripheral swelling, scrotal edema, lymphedema, swelling, and localized edema] | 11 | 0 | 9 | 0
Injury, poisoning and procedural complications
Fall | 16 | 1.7 | 9 | 0.8
Fracture [Includes rib fracture, lumbar vertebral fracture, spinal compression fracture, spinal fracture, foot fracture, hip fracture, humerus fracture, thoracic vertebral fracture, upper limb fracture, fractured sacrum, hand fracture, pubis fracture, acetabulum fracture, ankle fracture, compression fracture, costal cartilage fracture, facial bones fracture, lower limb fracture, osteoporotic fracture, wrist fracture, avulsion fracture, fibula fracture, fractured coccyx, pelvic fracture, radius fracture, sternal fracture, stress fracture, traumatic fracture, cervical vertebral fracture, femoral neck fracture, and tibia fracture] | 12 | 2.7 | 7 | 0.8
Investigations
Weight decreased | 16 | 1.1 | 6 | 0.3
Vascular disorders
Hypertension | 25 | 14 | 20 | 12
Hot flush | 14 | 0 | 9 | 0
Gastrointestinal disorders
Diarrhea | 20 | 1.1 | 15 | 0.5
Nausea | 18 | 0 | 16 | 0

Additional clinically significant adverse reactions occurring in less than 10% of patients treated with ERLEADA included hypothyroidism (8% versus 2% on placebo), pruritus (6% versus 1.5% on placebo), heart failure (2.2% versus 1% on placebo), and ILD/pneumonitis (0.6% versus 0% on placebo).

Table 4: Laboratory Abnormalities Occurring in ≥ 15% of ERLEADA-Treated Patients and at a Higher Incidence than Placebo (Between Arm Difference > 5% All Grades) in SPARTAN (nmCRPC)
 | ERLEADA N=803 |  | Placebo N=398
Laboratory Abnormality | All Grades % | Grade 3–4 % | All Grades % | Grade 3–4 %
Hematology
Anemia | 70 | 0.4 | 64 | 0.5
Leukopenia | 47 | 0.3 | 29 | 0
Lymphopenia | 41 | 1.8 | 21 | 1.6
Chemistry
Hypercholesterolemia [Does not reflect fasting values] | 76 | 0.1 | 46 | 0
Hyperglycemia | 70 | 2 | 59 | 1.0
Hypertriglyceridemia | 67 | 1.6 | 49 | 0.8
Hyperkalemia | 32 | 1.9 | 22 | 0.5

Rash

In the combined data of two randomized, placebo-controlled clinical studies, SPARTAN and TITAN, rash associated with ERLEADA was most commonly described as macular or maculo-papular. Adverse reactions of rash were reported for 26% of patients treated with ERLEADA versus 8% of patients treated with placebo. Grade 3 rashes (defined as covering > 30% body surface area [BSA]) were reported with ERLEADA treatment (6%) versus placebo (0.5%).

The onset of rash occurred at a median of 83 days of ERLEADA treatment. Rash resolved in 78% of patients within a median of 78 days from onset of rash. Rash was commonly managed with oral antihistamines, topical corticosteroids, and 19% of patients received systemic corticosteroids. Dose reduction or dose interruption occurred in 14% and 28% of patients, respectively. Of the patients who had dose interruption, 59% experienced recurrence of rash upon reintroduction of ERLEADA.

Hypothyroidism

In the combined data of two randomized, placebo-controlled clinical studies, SPARTAN and TITAN, hypothyroidism was reported for 8% of patients treated with ERLEADA and 1.5% of patients treated with placebo based on assessments of thyroid-stimulating hormone (TSH) every 4 months. Elevated TSH occurred in 25% of patients treated with ERLEADA and 7% of patients treated with placebo. The median onset was at the first scheduled assessment. There were no Grade 3 or 4 adverse reactions. Thyroid replacement therapy was initiated in 4.9% of patients treated with ERLEADA. Thyroid replacement therapy, when clinically indicated, should be initiated or dose-adjusted [see Drug Interactions (7.2)] .

6.2 Post-Marketing Experience

The following additional adverse reactions have been identified during post-approval use of ERLEADA. Because these reactions are reported voluntarily from a population of uncertain size, it is not always possible to reliably estimate the frequency or establish a causal relationship to drug exposure.

Respiratory, Thoracic and Mediastinal Disorders:interstitial lung disease/pneumonitis [see Warnings and Precautions (5.6)]

Skin and Subcutaneous Tissue Disorders:Stevens-Johnson syndrome/toxic epidermal necrolysis (SJS/TEN) and drug reaction with eosinophilia and systemic symptoms (DRESS).

7 DRUG INTERACTIONS

7.1 Effect of Other Drugs on ERLEADA

Strong CYP2C8 or CYP3A4 Inhibitors

Co-administration of a strong CYP2C8 or CYP3A4 inhibitor is predicted to increase the steady-state exposure of the active moieties (sum of unbound apalutamide plus the potency-adjusted unbound N-desmethyl-apalutamide). No initial dose adjustment is necessary however, reduce the ERLEADA dose based on tolerability [see Dosage and Administration (2.2)] . Mild or moderate inhibitors of CYP2C8 or CYP3A4 are not expected to affect the exposure of apalutamide.

7.2 Effect of ERLEADA on Other Drugs

CYP3A4, CYP2C9, CYP2C19 and UGT Substrates

ERLEADA is a strong inducer of CYP3A4 and CYP2C19, and a weak inducer of CYP2C9 in humans. Concomitant use of ERLEADA with medications that are primarily metabolized by CYP3A4, CYP2C19, or CYP2C9 can result in lower exposure to these medications. Substitution for these medications is recommended when possible or evaluate for loss of activity if medication is continued. Concomitant administration of ERLEADA with medications that are substrates of UDP-glucuronosyl transferase (UGT) can result in decreased exposure. Use caution if substrates of UGT must be co-administered with ERLEADA and evaluate for loss of activity [see Clinical Pharmacology (12.3)] .

P-gp, BCRP or OATP1B1 Substrates

Apalutamide was shown to be a weak inducer of P-glycoprotein (P-gp), breast cancer resistance protein (BCRP), and organic anion transporting polypeptide 1B1 (OATP1B1) clinically. At steady-state, apalutamide reduced the plasma exposure to fexofenadine (a P-gp substrate) and rosuvastatin (a BCRP/OATP1B1 substrate). Concomitant use of ERLEADA with medications that are substrates of P-gp, BCRP, or OATP1B1 can result in lower exposure of these medications. Use caution if substrates of P-gp, BCRP or OATP1B1 must be co-administered with ERLEADA and evaluate for loss of activity if medication is continued [see Clinical Pharmacology (12.3)] .

8 USE IN SPECIFIC POPULATIONS

8.1 Pregnancy

Risk Summary

The safety and efficacy of ERLEADA have not been established in females. Based on findings from animals and its mechanism of action, ERLEADA can cause fetal harm and loss of pregnancy when administered to a pregnant female [see Clinical Pharmacology (12.1)] . There are no available data on ERLEADA use in pregnant women to inform a drug-associated risk. In an animal reproduction study, oral administration of apalutamide to pregnant rats during and after organogenesis resulted in fetal abnormalities and embryo-fetal lethality at maternal exposures ≥ 2 times the human clinical exposure (AUC) at the recommended dose (see Data) .

Data

Animal Data

In a pilot embryo-fetal developmental toxicity study in rats, apalutamide caused developmental toxicity when administered at oral doses of 25, 50 or 100 mg/kg/day throughout and after the period of organogenesis (gestational days 6–20). Findings included embryo-fetal lethality (resorptions) at doses ≥50 mg/kg/day, decreased fetal anogenital distance, misshapen pituitary gland, and skeletal variations (unossified phalanges, supernumerary short thoracolumbar rib(s), and small, incomplete ossification, and/or misshapen hyoid bone) at ≥25 mg/kg/day. A dose of 100 mg/kg/day caused maternal toxicity. The doses tested in rats resulted in systemic exposures (AUC) approximately 2, 4 and 6 times, respectively, the AUC in patients.

8.2 Lactation

Risk Summary

The safety and efficacy of ERLEADA have not been established in females. There are no data on the presence of apalutamide or its metabolites in human milk, the effect on the breastfed child, or the effect on milk production.

8.3 Females and Males of Reproductive Potential

Contraception

Males

Based on the mechanism of action and findings in an animal reproduction study, advise male patients with female partners of reproductive potential to use effective contraception during treatment and for 3 months after the last dose of ERLEADA [see Use in Specific Populations (8.1)] .

Infertility

Males

Based on animal studies, ERLEADA may impair fertility in males of reproductive potential [see Nonclinical Toxicology (13.1)] .

8.4 Pediatric Use

Safety and effectiveness of ERLEADA in pediatric patients have not been established.

8.5 Geriatric Use

Of the 1327 patients who received ERLEADA in clinical studies, 19% of patients were less than 65 years, 41% of patients were 65 years to 74 years, and 40% were 75 years and over.

No overall differences in effectiveness were observed between older and younger patients.

Of patients treated with ERLEADA (n=1073), Grade 3–4 adverse reactions occurred in 39% of patients younger than 65 years, 41% of patients 65–74 years, and 49% of patients 75 years or older. Falls in patients receiving ERLEADA with androgen deprivation therapy was elevated in the elderly, occurring in 8% of patients younger than 65 years, 10% of patients 65–74 years, and 19% of patients 75 years or older.

10 OVERDOSAGE

There is no known specific antidote for apalutamide overdose. In the event of an overdose, stop ERLEADA, undertake general supportive measures until clinical toxicity has been diminished or resolved.

11 DESCRIPTION

Apalutamide, the active ingredient of ERLEADA, is an androgen receptor inhibitor. Each ERLEADA tablet contains either 60 mg or 240 mg of apalutamide. The chemical name is (4-[7-(6-Cyano-5-trifluoromethylpyridin-3-yl)-8-oxo-6-thioxo-5,7-diazaspiro[3.4]oct-5-yl]-2-fluoro-N-methylbenzamide). Apalutamide is a white to slightly yellow powder. Apalutamide is practically insoluble in aqueous media over a wide range of pH values.

The molecular weight is 477.44 and molecular formula is C21H15F4N5O2S. The structural formula is:

ERLEADA®(apalutamide) tablets are available in 240 mg tablets and 60 mg tablets with the following inactive ingredients:

- 240 mg film-coated tablets: colloidal anhydrous silica, croscarmellose sodium, hydroxypropyl methylcellulose-acetate succinate, silicified microcrystalline cellulose, and magnesium stearate. The coating contains glyceryl monocaprylocaprate, iron oxide black, polyvinyl alcohol, talc, titanium dioxide, and vinyl alcohol grafted copolymer.
- 60 mg film-coated tablets: colloidal anhydrous silica, croscarmellose sodium, hydroxypropyl methylcellulose-acetate succinate, magnesium stearate, microcrystalline cellulose, and silicified microcrystalline cellulose. The coating contains iron oxide black, iron oxide yellow, polyethylene glycol, polyvinyl alcohol, talc, and titanium dioxide.

12 CLINICAL PHARMACOLOGY

12.1 Mechanism of Action

Apalutamide is an Androgen Receptor (AR) inhibitor that binds directly to the ligand-binding domain of the AR. Apalutamide inhibits AR nuclear translocation, inhibits DNA binding, and impedes AR-mediated transcription. A major metabolite, N-desmethyl apalutamide, is a less potent inhibitor of AR, and exhibited one-third the activity of apalutamide in an in vitrotranscriptional reporter assay. Apalutamide administration caused decreased tumor cell proliferation and increased apoptosis leading to decreased tumor volume in mouse xenograft models of prostate cancer.

12.2 Pharmacodynamics

Apalutamide 240 mg daily in addition to ADT in patients with mCSPC (TITAN) reduced PSA to undetectable levels (<0.2 ng/mL) in 68% of patients compared to 32% of patients taking ADT alone.

Apalutamide 240 mg daily in addition to ADT in patients with nmCRPC (SPARTAN) reduced PSA to undetectable levels (<0.2 ng/mL) in 38% of patients compared to no patients (0%) taking ADT alone.

The exposure-response relationship and time course of pharmacodynamic response for the safety and effectiveness of apalutamide have not been fully characterized.

Cardiac Electrophysiology

The effect of apalutamide 240 mg once daily on the QTc interval was assessed in an open-label, uncontrolled, multi-center, single-arm dedicated QT study in 45 patients with CRPC. The maximum mean QTcF change from baseline was 12.4 ms (2-sided 90% upper CI: 16.0 ms). An exposure-QT analysis suggested a concentration-dependent increase in QTcF for apalutamide and its active metabolite.

12.3 Pharmacokinetics

Apalutamide pharmacokinetic parameters are presented as the mean [standard deviation (SD)] unless otherwise specified. Apalutamide Cmaxand area under the concentration curve (AUC) increased proportionally following repeated once-daily dosing of 30 to 480 mg (0.125 to 2 times the recommended dosage). Following administration of the recommended dosage, apalutamide steady-state was achieved after 4 weeks and the mean accumulation ratio was approximately 5-fold. Apalutamide Cmaxwas 6.0 mcg/mL (1.7) and AUC was 100 mcg∙h/mL (32) at steady-state. Daily fluctuations in apalutamide plasma concentrations were low, with mean peak-to-trough ratio of 1.63. An increase in apparent clearance (CL/F) was observed with repeat dosing, likely due to induction of apalutamide's own metabolism. The auto-induction effect likely reached its maximum at the recommended dosage because exposure of apalutamide across the dose range of 30 to 480 mg is dose-proportional.

The major active metabolite N-desmethyl apalutamide Cmaxwas 5.9 mcg/mL (1.0) and AUC was 124 mcg∙h/mL (23) at steady-state after the recommended dosage. N-desmethyl apalutamide was characterized by a flat concentration-time profile at steady-state with a mean peak-to-trough ratio of 1.27. Mean AUC metabolite/parent drug ratio for N-desmethyl apalutamide following repeat-dose administration was 1.3. Based on systemic exposure, relative potency, and pharmacokinetic properties, N-desmethyl apalutamide likely contributed to the clinical activity of apalutamide.

Absorption

Mean absolute oral bioavailability was approximately 100%. Median time to achieve peak plasma concentration (tmax) was 2 hours (range: 1 to 5 hours).

Oral administration of four 60 mg apalutamide tablets dispersed in applesauce resulted in no clinically relevant changes in Cmaxand AUC when compared to administration of four intact 60 mg tablets under fasting condition.

Effect of Food

Administration of apalutamide to healthy subjects under fasting conditions and with a high-fat meal (approximately 500 to 600 fat calories, 250 carbohydrate calories, and 150 protein calories) resulted in no clinically relevant changes in Cmaxand AUC. Median time to reach tmaxwas delayed approximately 2 hours with food.

Distribution

The mean apparent volume of distribution at steady-state of apalutamide was approximately 276 L.

Apalutamide was 96% and N-desmethyl apalutamide was 95% bound to plasma proteins with no concentration dependency.

Elimination

The CL/F of apalutamide was 1.3 L/h after single dosing and increased to 2.0 L/h at steady-state after once-daily dosing likely due to CYP3A4 auto-induction. The mean effective half-life for apalutamide in patients was approximately 3 days at steady-state.

Metabolism

Metabolism is the main route of elimination of apalutamide. Apalutamide is primarily metabolized by CYP2C8 and CYP3A4 to form active metabolite, N-desmethyl apalutamide. The contribution of CYP2C8 and CYP3A4 in the metabolism of apalutamide is estimated to be 58% and 13% following single dose but changes to 40% and 37%, respectively at steady-state.

Apalutamide represented 45% and N-desmethyl apalutamide represented 44% of the total AUC following a single oral administration of radiolabeled apalutamide 240 mg.

Excretion

Up to 70 days following a single oral administration of radiolabeled apalutamide, 65% of the dose was recovered in urine (1.2% of dose as unchanged apalutamide and 2.7% as N-desmethyl apalutamide) and 24% was recovered in feces (1.5% of dose as unchanged apalutamide and 2% as N-desmethyl apalutamide).

Specific Populations

No clinically significant differences in the pharmacokinetics of apalutamide or N-desmethyl apalutamide were observed based on age (18–94 years), race (Black, non-Japanese Asian, Japanese), mild to moderate (eGFR 30–89 mL/min/1.73 m^2, estimated by the modification of diet in renal disease [MDRD] equation) renal impairment, or mild (Child-Pugh A) to moderate (Child-Pugh B) hepatic impairment.

The effect of severe renal impairment or end stage renal disease (eGFR ≤29 mL/min/1.73 m^2, MDRD) or severe hepatic impairment (Child-Pugh C) on apalutamide pharmacokinetics is unknown.

Drug Interactions

Effect of Other Drugs on ERLEADA

Strong CYP2C8 inhibitors

Apalutamide Cmaxdecreased by 21% while AUC increased by 68% following co-administration of ERLEADA as a 240 mg single dose with gemfibrozil (a strong CYP2C8 inhibitor). Gemfibrozil is predicted to increase the steady-state apalutamide Cmaxby 32% and AUC by 44%. For the active moieties (sum of unbound apalutamide plus the potency-adjusted unbound N-desmethyl apalutamide), the predicted steady-state Cmaxincreased by 19% and AUC by 23%.

Strong CYP3A4 inhibitors

Apalutamide Cmaxdecreased by 22% while AUC was similar following co-administration of ERLEADA as a 240 mg single dose with itraconazole (a strong CYP3A4 inhibitor). Ketoconazole (a strong CYP3A4 inhibitor) is predicted to increase the single-dose apalutamide AUC by 24% but have no impact on Cmax. Ketoconazole is predicted to increase the steady-state apalutamide Cmaxby 38% and AUC by 51%. For the active moieties, the predicted steady-state Cmaxincreased by 23% and AUC by 28%.

CYP3A4/CYP2C8 inducers

Rifampin (a strong CYP3A4 and moderate CYP2C8 inducer) is predicted to decrease the steady-state apalutamide Cmaxby 25% and AUC by 34%. For the active moieties, the predicted steady-state Cmaxdecreased by 15% and AUC by 19%.

Acid lowering agents

Apalutamide is not ionizable under relevant physiological pH condition, therefore acid lowering agents (e.g., proton pump inhibitor, H2-receptor antagonist, antacid) are not expected to affect the solubility and bioavailability of apalutamide.

Drugs affecting transporters

In vitro, apalutamide and N-desmethyl apalutamide are substrates for P-gp but not BCRP, OATP1B1, and OATP1B3. Because apalutamide is completely absorbed after oral administration, P-gp does not limit the absorption of apalutamide and therefore, inhibition or induction of P-gp is not expected to affect the bioavailability of apalutamide.

Effect of ERLEADA on Other Drugs

CYP substrates

In vitrostudies showed that apalutamide and N-desmethyl apalutamide are moderate to strong CYP3A4 and CYP2B6 inducers, are moderate inhibitors of CYP2B6 and CYP2C8, and weak inhibitors of CYP2C9, CYP2C19, and CYP3A4. Apalutamide and N-desmethyl apalutamide do not affect CYP1A2 and CYP2D6 at therapeutically relevant concentrations.

Co-administration of ERLEADA with single oral doses of sensitive CYP substrates resulted in a 92% decrease in the AUC of midazolam (a CYP3A4 substrate), 85% decrease in the AUC of omeprazole (a CYP2C19 substrate), and 46% decrease in the AUC of S-warfarin (a CYP2C9 substrate). ERLEADA did not cause clinically significant changes in exposure to a CYP2C8 substrate.

P-gp, BCRP and OATP1B1 substrates

Co-administration of ERLEADA with single oral doses of transporter substrates resulted in a 30% decrease in the AUC of fexofenadine (a P-gp substrate) and 41% decrease in the AUC of rosuvastatin (a BCRP/OATP1B1 substrate) but had no impact on Cmax.

UGT substrates

Apalutamide may induce UGT. Concomitant administration of ERLEADA with medications that are substrates of UGT may result in lower exposure to these medications.

OCT2, OAT1, OAT3 and MATEs substrates

In vitro, apalutamide and N-desmethyl apalutamide inhibit organic cation transporter 2 (OCT2), organic anion transporter 3 (OAT3) and multidrug and toxin extrusions (MATEs), and do not inhibit organic anion transporter 1. Apalutamide is not predicted to cause clinically significant changes in exposure to an OAT3 substrate.

GnRH analog

In mCSPC subjects receiving leuprolide acetate (a GnRH analog) co-administered with apalutamide, PK data indicated that apalutamide had no apparent effect on the steady-state exposure of leuprolide.

13 NONCLINICAL TOXICOLOGY

13.1 Carcinogenesis, Mutagenesis, Impairment of Fertility

In a 2-year carcinogenicity study in male rats, apalutamide was administered by oral gavage at doses of 5, 15 and 50 mg/kg/day. Apalutamide increased the incidence of Leydig interstitial cell adenoma in the testes at doses ≥ 5 mg/kg/day (0.2 times the human exposure based on AUC). The findings in the testes are considered to be related to the pharmacological activity of apalutamide. Rats are regarded as more sensitive than humans to developing interstitial cell tumors in the testes. Oral administration of apalutamide to male rasH2 transgenic mice for 6 months did not result in increased incidence of neoplasms at doses up to 30 mg/kg/day.

Apalutamide did not induce mutations in the bacterial reverse mutation (Ames) assay and was not genotoxic in either in vitrochromosome aberration assay or the in vivorat bone marrow micronucleus assay or the in vivorat Comet assay.

In repeat-dose toxicity studies in male rats (up to 26 weeks) and dogs (up to 39 weeks), atrophy of the prostate gland and seminal vesicles, aspermia/hypospermia, tubular degeneration and/or hyperplasia or hypertrophy of the interstitial cells in the reproductive system were observed at ≥ 25 mg/kg/day in rats (1.4 times the human exposure based on AUC) and ≥ 2.5 mg/kg/day in dogs (0.9 times the human exposure based on AUC).

In a fertility study in male rats, a decrease in sperm concentration and motility, increased abnormal sperm morphology, lower copulation and fertility rates (upon pairing with untreated females) along with reduced weights of the secondary sex glands and epididymis were observed following 4 weeks of dosing at ≥ 25 mg/kg/day (0.8 times the human exposure based on AUC). A reduced number of live fetuses due to increased pre- and/or post-implantation loss was observed following 4 weeks of 150 mg/kg/day administration (5.7 times the human exposure based on AUC). Effects on male rats were reversible after 8 weeks from the last apalutamide administration.

14 CLINICAL STUDIES

The efficacy and safety of ERLEADA was established in two randomized placebo-controlled clinical trials.

TITAN (NCT02489318): Metastatic Castration-sensitive Prostate Cancer (mCSPC)

TITAN was a randomized, double-blind, placebo-controlled, multinational, clinical trial in which 1052 patients with mCSPC were randomized (1:1) to receive either ERLEADA orally at a dose of 240 mg once daily (N=525) or placebo once daily (N=527). All patients in the TITAN trial received concomitant GnRH analog or had prior bilateral orchiectomy. Patients were stratified by Gleason score at diagnosis, prior docetaxel use, and region of the world. Patients with both high- and low-volume mCSPC were eligible for the study. High volume of disease was defined as metastases involving the viscera with 1 bone lesion or the presence of 4 or more bone lesions, at least 1 of which must be in a bony structure beyond the vertebral column and pelvic bones.

The following patient demographics and baseline disease characteristics were balanced between the treatment arms. The median age was 68 years (range 43–94) and 23% of patients were 75 years of age or older. The racial distribution was 68% Caucasian, 22% Asian, and 2% Black. Sixty-three percent (63%) of patients had high-volume disease and 37% had low-volume disease. Sixteen percent (16%) of patients had prior surgery, radiotherapy of the prostate or both. A majority of patients had a Gleason score of 8 or higher (67%). Sixty-eight percent (68%) of patients received prior treatment with an anti-androgen (bicalutamide, flutamide, or nilutamide). All patients except one in the placebo group, had an Eastern Cooperative Oncology Group Performance Status (ECOG PS) score of 0 or 1 at study entry.

The major efficacy outcome measures of the study were overall survival (OS) and radiographic progression-free survival (rPFS). Radiographic progression-free survival was based on investigator assessment and was defined as time from randomization to radiographic disease progression or death. Radiographic disease progression was defined by identification of 2 or more new bone lesions on a bone scan with confirmation (Prostate Cancer Working Group 2 criteria) and/or progression in soft tissue disease.

A statistically significant improvement in OS and rPFS was demonstrated in patients randomized to receive ERLEADA compared with patients randomized to receive placebo. The results for OS are based upon a prespecified interim efficacy analysis. An updated OS analysis was conducted at the time of final study analysis when 405 deaths were observed. The median follow-up time was 44 months. Thirty-nine percent of patients in the placebo arm crossed over to receive ERLEADA. Efficacy results of TITAN are summarized in Table 5 and Figures 1 and 2.

Table 5: Efficacy Results from the TITAN Study
Endpoint | ERLEADA (N=525) | Placebo (N=527)
Primary Overall Survival [Interim analysis is based on 50% of the number of events planned for the final analysis. Allocated alpha = 0.01.]
Deaths (%) | 83 (16%) | 117 (22%)
Median, months (95% CI) [NE=Not Estimable] | NE (NE, NE) | NE (NE, NE)
Hazard Ratio (95% CI) [Hazard ratio is from stratified proportional hazards model. Hazard ratio <1 favors ERLEADA.] | 0.67 (0.51, 0.89)
p-value [p-value is from the log-rank test stratified by Gleason score at diagnosis (≤7 vs. >7), Region (NA/EU vs. Other Countries) and Prior docetaxel use (Yes vs. No).] | 0.0053
Updated Overall Survival
Deaths (%) | 170 (32%) | 235 (45%)
Median, months (95% CI) | NE (NE, NE) | 52 (42, NE)
Hazard Ratio (95% CI) | 0.65 (0.53, 0.79)
Radiographic Progression-free Survival
Disease progression or death (%) | 134 (26%) | 231 (44%)
Median, months (95% CI) | NE (NE, NE) | 22.1 (18, 33)
Hazard Ratio (95% CI) | 0.48 (0.39, 0.60)
p-value | <0.0001

Consistent improvement in rPFS was observed across the following patient subgroups: disease volume (high vs low), prior docetaxel use (yes or no), and Gleason score at diagnosis (≤7 vs. >7).

Consistent improvement in OS was observed across the following patient subgroups: disease volume (high vs low) and Gleason score at diagnosis (≤7 vs. >7).

Treatment with ERLEADA resulted in a statistically significant delay in the initiation of cytotoxic chemotherapy (HR = 0.39, 95% CI = 0.27, 0.56; p < 0.0001).

Figure 1: Kaplan-Meier Plot of Updated Overall Survival (OS); Intent-to-treat mCSPC Population (TITAN)

Figure 2: Kaplan-Meier Plot of Radiographic Progression-Free Survival (rPFS); Intent-to-treat mCSPC Population (TITAN)

SPARTAN (NCT01946204): Non-metastatic, Castration-resistant Prostate Cancer (nmCRPC)

SPARTAN was a multicenter, double-blind, randomized (2:1), placebo-controlled clinical trial in which 1207 patients with nmCRPC were randomized (2:1) to receive either ERLEADA orally at a dose of 240 mg once daily (N=806) or placebo once daily (N=401). All patients in the SPARTAN trial received a concomitant GnRH analog or had a bilateral orchiectomy. Patients were stratified by Prostate Specific Antigen (PSA) Doubling Time (PSADT), the use of bone-sparing agents, and locoregional disease. Patients were required to have a PSADT ≤ 10 months and confirmation of non-metastatic disease by blinded independent central review (BICR). PSA results were blinded and were not used for treatment discontinuation. Patients randomized to either arm discontinued treatment for radiographic disease progression confirmed by BICR, locoregional-only progression, initiation of new treatment, unacceptable toxicity, or withdrawal.

The following patient demographics and baseline disease characteristics were balanced between the treatment arms. The median age was 74 years (range 48–97) and 26% of patients were 80 years of age or older. The racial distribution was 66% Caucasian, 12% Asian, and 6% Black. Seventy-seven percent (77%) of patients in both treatment arms had prior surgery or radiotherapy of the prostate. A majority of patients had a Gleason score of 7 or higher (78%). Fifteen percent (15%) of patients had <2 cm pelvic lymph nodes at study entry. Seventy-three percent (73%) of patients received prior treatment with an anti-androgen; 69% of patients received bicalutamide and 10% of patients received flutamide. All patients had an Eastern Cooperative Oncology Group Performance Status (ECOG PS) score of 0 or 1 at study entry.

The major efficacy outcome measure of the study was metastasis-free survival (MFS), defined as the time from randomization to the time of first evidence of BICR-confirmed distant metastasis, defined as new bone or soft tissue lesions or enlarged lymph nodes above the iliac bifurcation, or death due to any cause, whichever occurred first. Additional efficacy endpoints were time to metastasis (TTM), progression-free survival (PFS) which also includes locoregional progression, time to symptomatic progression, overall survival (OS), and time to initiation of cytotoxic chemotherapy.

A statistically significant improvement in MFS and OS was demonstrated in patients randomized to receive ERLEADA compared with patients randomized to receive placebo. The major efficacy outcome (MFS) was supported by improvements in TTM and PFS. The final analysis of OS and time to initiation of cytotoxic chemotherapy was conducted 32 months after the analysis of MFS, TTM and PFS. The efficacy results from SPARTAN are summarized in Table 6 and Figures 3 and 4.

Table 6: Efficacy Results from the SPARTAN Study
Endpoint | ERLEADA (N=806) | Placebo (N=401)
Metastasis Free Survival [All analyses stratified by PSA doubling time, bone-sparing agent use, and locoregional disease status.] , [Confirmed responses assessed by BICR.] , [Locoregional-only progression is observed in 2.4% of patients overall.]
Number of Events (%) | 184 (23%) | 194 (48%)
Median, months (95% CI) [NE=Not Estimable] | 40.5 (NE, NE) | 16.2 (15, 18)
Hazard Ratio (95% CI) | 0.28 (0.23, 0.35)
p-value | <0.0001
Time to Metastasis,
Number of Events (%) | 175 (22%) | 191 (48%)
Median, months (95% CI) | 40.5 (NE, NE) | 16.6 (15, 18)
Hazard Ratio (95% CI) | 0.27 (0.22, 0.34)
p-value | <0.0001
Progression-Free Survival,
Number of Events (%) | 200 (25%) | 204 (51%)
Median, months (95% CI) | 40.5 (NE, NE) | 14.7 (14, 18)
Hazard Ratio (95% CI) | 0.29 (0.24, 0.36)
p-value | <0.0001
Overall Survival
Number of Events (%) | 274 (34%) | 154 (38%)
Median, months (95% CI) | 73.9 (61, NE) | 59.9 (53, NE)
Hazard Ratio (95% CI) | 0.78 (0.64, 0.96)
p-value | 0.0161

Consistent results for MFS were observed across patient subgroups including PSADT (≤ 6 months or > 6 months), use of a prior bone-sparing agent (yes or no), and locoregional disease (N0 or N1).

Treatment with ERLEADA resulted in a statistically significant delay in the initiation of cytotoxic chemotherapy [HR = 0.63 (95% CI:0.49, 0.81), p=0.0002].

Figure 3: Kaplan-Meier Metastasis-Free Survival (MFS) Curve in SPARTAN (nmCRPC)

Figure 4: Kaplan-Meier Overall Survival (OS) Curve in SPARTAN (nmCRPC)

16 HOW SUPPLIED/STORAGE AND HANDLING

ERLEADA®(apalutamide) tablets are available in the strengths and packages listed below:

- ERLEADA®240 mg Tablets
  Film coated, bluish grey to grey, oval-shaped tablets debossed with "E240" on one side.
  NDC Number 59676‐604‐30 - 30 tablets available in bottles with a silica gel desiccant and has a child-resistant closure

- ERLEADA®60 mg Tablets
  Film coated, slightly yellowish to greyish green, oblong-shaped tablets debossed with "AR 60" on one side.
  NDC Number 59676‐600‐12 - 120 tablets available in bottles with a silica gel desiccant and has a child-resistant closure

Storage and Handling

Store at 20 °C to 25 °C (68 °F to 77 °F); excursions permitted to 15 °C to 30 °C (59 °F to 86 °F) [see USP Controlled Room Temperature].

Store in original package to protect from light and moisture. Do not discard desiccant.

17 PATIENT COUNSELING INFORMATION

Advise the patient to read the FDA-approved patient labeling (Patient Information and Instructions for Use).

Cerebrovascular and Ischemic Cardiovascular Events

- Inform patients that ERLEADA has been associated with cerebrovascular and ischemic cardiovascular events. Advise patients to seek immediate medical attention if any symptoms suggestive of a cardiovascular or a cerebrovascular event occur [see Warnings and Precautions (5.1)] .

Falls and Fractures

- Inform patients that ERLEADA is associated with an increased incidence of falls and fractures [see Warnings and Precautions (5.2, 5.3)] .

Seizures

- Inform patients that ERLEADA has been associated with an increased risk of seizure. Discuss conditions that may predispose to seizures and medications that may lower the seizure threshold. Advise patients of the risk of engaging in any activity where sudden loss of consciousness could cause serious harm to themselves or others. Inform patients to contact their healthcare provider right away if they experience a seizure [see Warnings and Precautions (5.4)] .

Severe Cutaneous Adverse Reactions (SCARs)

- Inform patients that ERLEADA has been associated with SCARs (including SJS/TEN and DRESS), which can be fatal or life-threatening. Advise patients to stop taking ERLEADA and contact their healthcare provider or seek medical attention right away if they experience signs or symptoms of SCARs [see Warnings and Precautions (5.5)] .

Interstitial Lung Disease (ILD)/Pneumonitis

- Inform patients of the risks of fatal or life-threatening ILD/pneumonitis. Advise patients to stop taking ERLEADA and contact their healthcare provider or seek medical attention immediately if they develop new or worsening respiratory symptoms [see Warnings and Precautions (5.6)] .

Rash

- Inform patients that ERLEADA is associated with rashes and to inform their healthcare provider if they develop a rash [see Adverse Reactions (6.1, 6.2)] .

Dosage and Administration

- Inform patients receiving concomitant gonadotropin-releasing hormone (GnRH) analog therapy that they need to maintain this treatment during the course of treatment with ERLEADA.
- Instruct patients to take their dose at the same time each day (once daily). ERLEADA can be taken with or without food. Each tablet should be swallowed whole. Do not crush or split tablets [see Dosage and Administration (2.1)] .
- Instruct patients who cannot swallow tablets whole to follow the instructions for the prescribed strength of ERLEADA tablets for alternate methods of administration, including administration through a feeding tube [see Dosage and Administration (2.3)] .
- Inform patients that in the event of a missed daily dose of ERLEADA, they should take their normal dose as soon as possible on the same day with a return to the normal schedule on the following day. The patient should not take extra tablets to make up the missed dose [see Dosage and Administration (2.1)] .

Embryo-Fetal Toxicity

- Inform patients that ERLEADA can be harmful to a developing fetus. Advise male patients with female partners of reproductive potential to use effective contraception during treatment and for 3 months after the last dose of ERLEADA. Advise male patients to use a condom if having sex with a pregnant woman [see Warnings and Precautions (5.7)] .

Infertility

- Advise male patients that ERLEADA may impair fertility and not to donate sperm during therapy and for 3 months following the last dose of ERLEADA [see Use in Specific Populations (8.3)] .

Manufactured for:
Janssen Products, LP
Horsham, PA 19044, USA

For patent information: www.janssenpatents.com

© 2019, 2023 Janssen Pharmaceutical Companies

PATIENT INFORMATION
ERLEADA®(er lee'dah)
(apalutamide)
tablets

What is ERLEADA?
ERLEADA is a prescription medicine used for the treatment of prostate cancer:

- that has spread to other parts of the body and still responds to a medical or surgical treatment that lowers testosterone, OR
- that has not spread to other parts of the body and no longer responds to a medical or surgical treatment that lowers testosterone.

It is not known if ERLEADA is safe and effective in females.
It is not known if ERLEADA is safe and effective in children.

Before taking ERLEADA, tell your healthcare provider about all your medical conditions, including if you:

- have a history of heart disease
- have high blood pressure
- have diabetes
- have abnormal amounts of fat or cholesterol in your blood (dyslipidemia)
- have a history of seizures, brain injury, stroke, or brain tumors
- are pregnant or plan to become pregnant. ERLEADA can cause harm to your unborn baby and loss of pregnancy (miscarriage).
- have a partner who is pregnant or may become pregnant.
  - Males who have female partners who are able to become pregnant should use effective birth control (contraception) during treatment and for 3 months after the last dose of ERLEADA.
  - Males should use a condom during sex with a pregnant female.
  Talk with your healthcare provider if you have questions about birth control.
- are breastfeeding or plan to breastfeed. It is not known if ERLEADA passes into breast milk.

Tell your healthcare provider about all the medicines you take, including prescription and over-the-counter medicines, vitamins, and herbal supplements. ERLEADA can interact with many other medicines.
You should not start or stop any medicine before you talk with the healthcare provider that prescribed ERLEADA.
Know the medicines you take. Keep a list of them with you to show to your healthcare provider and pharmacist when you get a new medicine.

How should I take ERLEADA?

- Take ERLEADA exactly as your healthcare provider tells you.
- Do not stop taking your prescribed dose of ERLEADA without talking with your healthcare provider first.
- Take your prescribed dose of ERLEADA 1 time a day, at the same time each day.
- Take ERLEADA with or without food.
- Swallow ERLEADA tablets whole. Do notcrush or split the tablets.
- If you cannot swallow ERLEADA tablets whole or if you have a feeding tube, see the " Instructions for Use" for detailed instructions on how to prepare and take a dose of ERLEADA. ERLEADA comes in 2 different strengths (60 mg and 240 mg). Follow the instructions for your prescribed strength of ERLEADA.
- If you miss a dose of ERLEADA, take your normal dose as soon as possible on the same day. Return to your normal schedule on the following day. You should not take extra tablets to make up the missed dose.
- You should start or continue a gonadotropin-releasing hormone (GnRH) analog therapy during your treatment with ERLEADA unless you have had a surgery to lower the amount of testosterone in your body (surgical castration).
- If you take too much ERLEADA, call your healthcare provider or go to the nearest hospital emergency room.

What are the possible side effects of ERLEADA?
ERLEADA may cause serious side effects including:

- Heart disease, stroke, or mini-stroke.Bleeding in the brain or blockage of the arteries in the heart or in part of the brain have happened in some people during treatment with ERLEADA and can lead to death. Your healthcare provider will monitor you for signs and symptoms of heart or brain problems during your treatment with ERLEADA. Call your healthcare provider or get medical help right away if you get:

- chest pain or discomfort at rest or with activity
- shortness of breath
- numbness or weakness of the face, arm, or leg, especially on one side of the body

- trouble talking or understanding
- trouble seeing in one or both eyes
- dizziness, loss of balance or coordination, or trouble walking

- Fractures and falls.ERLEADA treatment can cause bones and muscles to weaken and may increase your risk for falls and fractures. Falls and fractures have happened in people during treatment with ERLEADA. Your healthcare provider will monitor your risks for falls and fractures during treatment with ERLEADA.
- Seizure.Treatment with ERLEADA may increase your risk of having a seizure. You should avoid activities where a sudden loss of consciousness could cause serious harm to yourself or others. Tell your healthcare provider right away if you have a loss of consciousness or seizure. Your healthcare provider will stop ERLEADA if you have a seizure during treatment.
- Severe skin reactions.Treatment with ERLEADA may cause severe skin reactions that can lead to death or be life-threatening. Stop taking ERLEADA and tell your healthcare provider or get medical help right away if you develop any of these signs or symptoms of a severe skin reaction:

- severe rash or rash that continues to get worse
- fever or flu-like symptoms
- swollen lymph nodes

- blisters or sores in the mouth, throat, nose, eyes, or genital area
- blistering or peeling of the skin

- Lung problems.Treatment with ERLEADA may cause inflammation of the lungs that can lead to death or be life-threatening. Stop taking ERLEADA and tell your healthcare provider or get medical help right away if you develop any new or worsening symptoms of lung problems, including:

- shortness of breath

- cough

- fever

The most common side effects of ERLEADA include:

- feeling very tired
- joint pain
- rash. Tell your healthcare provider if you get a rash.
- decreased appetite
- fall

- weight loss
- high blood pressure
- hot flash
- diarrhea
- fracture

Your healthcare provider may reduce your dose, temporarily stop, or permanently stop treatment with ERLEADA if you have certain side effects.
ERLEADA may cause fertility problems in males, which may affect the ability to father children. Talk to your healthcare provider if you have concerns about fertility. Do notdonate sperm during treatment with ERLEADA and for 3 months after the last dose of ERLEADA.
Tell your healthcare provider if you have any side effect that bothers you or that does not go away.
These are not all the possible side effects of ERLEADA.
Call your doctor for medical advice about side effects. You may report side effects to FDA at 1-800-FDA-1088.

How should I store ERLEADA?

- Store ERLEADA at room temperature between 68 °F to 77 °F (20 °C to 25 °C).
- ERLEADA comes in a child-resistant bottle.
- Store ERLEADA in the original package to protect from light and moisture.
- The bottle of ERLEADA contains a desiccant packet to help keep your medicine dry (protect it from moisture). Do not throw away (discard) the desiccant.

Keep ERLEADA and all medicines out of the reach of children.

General information about the safe and effective use of ERLEADA.
Medicines are sometimes prescribed for purposes other than those listed in a Patient Information leaflet. Do not use ERLEADA for a condition for which it was not prescribed. Do not give ERLEADA to other people, even if they have the same symptoms that you have. It may harm them. You can ask your healthcare provider or pharmacist for information about ERLEADA that is written for health professionals.

What are the ingredients in ERLEADA?
Active ingredient:apalutamide
Inactive ingredients:
240 mg film-coated tablets: colloidal anhydrous silica, croscarmellose sodium, hydroxypropyl methylcellulose-acetate succinate, silicified microcrystalline cellulose, and magnesium stearate. The coating contains glyceryl monocaprylocaprate, iron oxide black, polyvinyl alcohol, talc, titanium dioxide, and vinyl alcohol grafted copolymer.
60 mg film-coated tablets: colloidal anhydrous silica, croscarmellose sodium, hydroxypropyl methylcellulose-acetate succinate, magnesium stearate, microcrystalline cellulose, and silicified microcrystalline cellulose. The coating contains iron oxide black, iron oxide yellow, polyethylene glycol, polyvinyl alcohol, talc, and titanium dioxide.
Manufactured for:Janssen Products, LP, Horsham, PA 19044, USA
For patent information: www.janssenpatents.com
© 2019, 2023 Janssen Pharmaceutical Companies
For more information, call Janssen Products, LP at 1-800-526-7736 (1-800-JANSSEN) or go to www.erleada.com.

This Patient Information has been approved by the U.S. Food and Drug Administration.

Revised: 8/2024

INSTRUCTIONS FOR USE
ERLEADA®(er lee'dah)
(apalutamide)
tablets
This Instructions for Use contains information on how to prepare and take or give a dose of ERLEADA tablets if you cannot swallow ERLEADA tablets whole or if you have a feeding tube. Read this Instructions for Use before you prepare and take or give the first dose of ERLEADA, and each time you get a refill. Ask your healthcare provider or pharmacist if you have any questions.
Important information you need to know before preparing a dose of ERLEADA:
- ERLEADA comes in 2 different strengths, 60 mg tablets and 240 mg tablets. Please find the instructions below that refer to your prescribed ERLEADA strength for how to prepare and take or give ERLEADA tablets.
Preparing and taking ERLEADA if you cannot swallow tablets whole:
Preparing and taking ERLEADA 60 mg tablets by placing the tablets in non-carbonated water then mixing with orange juice, applesauce, or more non-carbonated water:
Step 1. | Place your entire prescribed dose of 60 mg tablets in a cup. Do not crush or split the tablets.
Step 2. | Add about 4 teaspoons (20 mL) of non-carbonated water to make sure that the tablets are completely covered in water.
Step 3. | Wait 2 minutes until the tablets are broken up and spread out, then stir the mixture.
Step 4. | Add 2 tablespoons (30 mL) of orange juice, applesauce, or non-carbonated water to the cup and stir the mixture.
Step 5. | Swallow the mixture right away.
Step 6. | Rinse the cup with enough non-carbonated water to make sure that you take your full dose of ERLEADA and drink it right away.
Do notstore ERLEADA that is mixed with non-carbonated water, orange juice, or applesauce for later use.
Preparing and taking ERLEADA 240 mg tablet by placing the tablet in non-carbonated water then mixing with orange juice, applesauce, or more non-carbonated water:
Step 1. | Place the whole 240 mg tablet in a cup. Do not crush or split the tablet.
Step 2. | Add about 2 teaspoons (10 mL) of non-carbonated water to make sure that the tablet is completely covered in water.
Step 3. | Wait 2 minutes until the tablet is broken up and spread out, then stir the mixture.
Step 4. | Add 2 tablespoons (30 mL) of orange juice, applesauce, or non-carbonated water to the cup and stir the mixture.
Step 5. | Swallow the mixture right away.
Step 6. | Rinse the cup with enough non-carbonated water to make sure that you take your full dose of ERLEADA and drink it right away.
Do notstore ERLEADA that is mixed with non-carbonated water, orange juice, or applesauce for later use.
Preparing and giving ERLEADA through a feeding tube:
Preparing and giving ERLEADA 60 mg tablets through a feeding tube 8 French or larger:
Step 1. | Remove the plunger out of the syringe (use at least a 50 mL syringe).
Step 2. | Add your entire prescribed dose of 60 mg tablets into the syringe body (barrel) and place the plunger back in the syringe. Do not crush or split the tablets.
Step 3. | Withdraw 20 mL of non-carbonated water into the syringe.
Step 4. | Wait 10 minutes and then shake the syringe very well (vigorously) to break the tablets apart completely.
Step 5. | Attach the syringe to the feeding tube and give the mixture right away.
Step 6. | Withdraw non-carbonated water into the same syringe and flush through the feeding tube. Repeat Step 6until no pieces of tablets are left in the syringe or feeding tube.
Preparing and giving ERLEADA 240 mg tablet through a feeding tube 8 French or larger:
Step 1. | Remove the plunger out of the syringe (use at least a 20 mL syringe).
Step 2. | Add one 240 mg tablet into the syringe body (barrel) and place the plunger back in the syringe. Do not crush or split the tablet.
Step 3. | Withdraw 10 mL of non-carbonated water into the syringe.
Step 4. | Wait 10 minutes and then shake the syringe very well (vigorously) to break the tablet apart completely.
Step 5. | Attach the syringe to the feeding tube and give the mixture right away.
Step 6. | Withdraw non-carbonated water into the same syringe and flush through the feeding tube. Repeat Step 6until no pieces of tablet are left in the syringe or feeding tube.
How should I store ERLEADA?
- Store ERLEADA at room temperature between 68 °F to 77 °F (20 °C to 25 °C).
- ERLEADA comes in a child-resistant bottle.
- Store ERLEADA in the original package to protect from light and moisture.
- The bottle of ERLEADA contains a desiccant packet to help keep your medicine dry (protect it from moisture). Do not throw away (discard) the desiccant.
Keep ERLEADA and all medicines out of the reach of children.
Manufactured for:Janssen Products, LP, Horsham, PA 19044, USA
For patent information: www.janssenpatents.com
© 2019, 2023 Janssen Pharmaceutical Companies
For more information, call Janssen Products, LP at 1-800-526-7736 (1-800-JANSSEN) or go to www.erleada.com.
This Instructions for Use has been approved by the U.S. Food and Drug Administration. |  | Revised: 07/2024

PRINCIPAL DISPLAY PANEL - 60 mg Tablet Bottle Label

NDC 59676-600-12

Erleada®
(apalutamide) tablets

60 mg

Each film-coated tablet
contains 60 mg of apalutamide.

This package is child-resistant.
Keep out of reach of children.

Rx only

120 film-coated
tablets

PRINCIPAL DISPLAY PANEL - 240 mg Tablet Bottle Label

NDC 59676-604-30

Erleada®
(apalutamide) tablets

240 mg

Each film-coated tablet contains
240 mg of apalutamide.

This package is child-resistant.
Keep out of reach of children.

Rx only

30 film-coated tablets